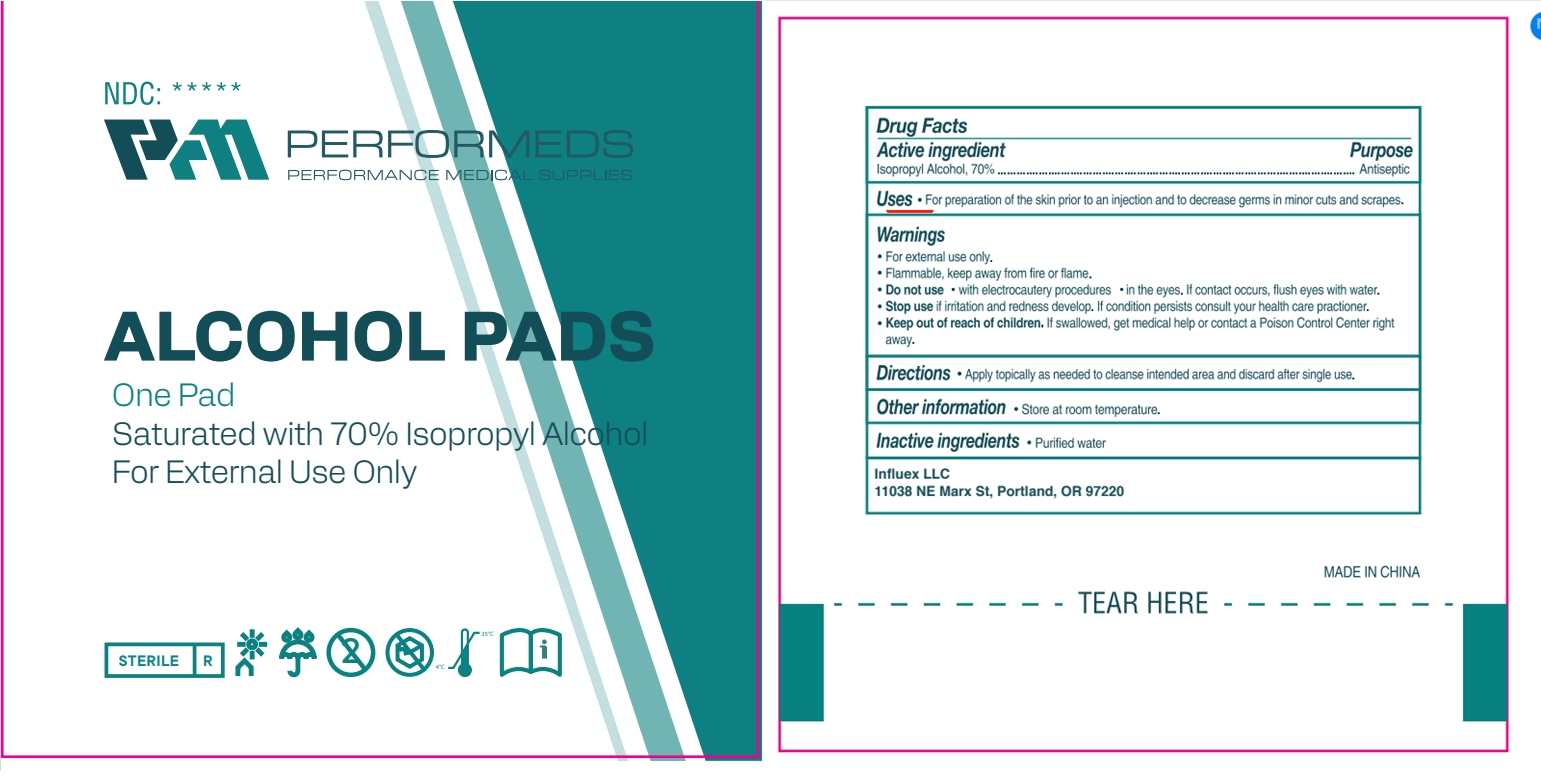 DRUG LABEL: Alcohol pads
NDC: 84449-001 | Form: PATCH
Manufacturer: SHENZHEN BENLIJU BIO-TECH CO.,LTD
Category: otc | Type: HUMAN OTC DRUG LABEL
Date: 20260105

ACTIVE INGREDIENTS: ISOPROPYL ALCOHOL 70 mL/100 mL
INACTIVE INGREDIENTS: WATER 30 mL/100 mL

ACTIVE INGREDIENT

lsopropyl Alcohol

PURPOSE

disinfect

INDICATIONS AND USAGE

For preparation of the skin prior to an injection and to decrease germs in minor cuts and scrapes

WARNINGS

*For extemal use only.
*Flammable. keep away from fire or flame.
*Do not use " with electrocautery procedures " in the eyes. lf contact occurs, flush eyes with water.
*Stop use if irritation and redness develop. If condition persists consult your health care practioner.

Keep out of reach of children, lf swallowed, get medical help or contact a Poison Control Center rightaway.

When using this product keep out of eyes, ears, and mouth. In case of contact with eyes, rinse eyes thoroughly with water.

Stop use and ask a doctor if irritation or rash occurs. These may be signs of a serious condition.

Keep out of reach of children. If swallowed, get medical help or contact a Poison Control Center right away.

DOSAGE AND ADMINISTRATION

For preparation of the skin prior to an injection and to decrease germs in minor cuts and scrapes.

STORAGE AND HANDLING

Store at room temperature.

INACTIVE INGREDIENT

Purified Water